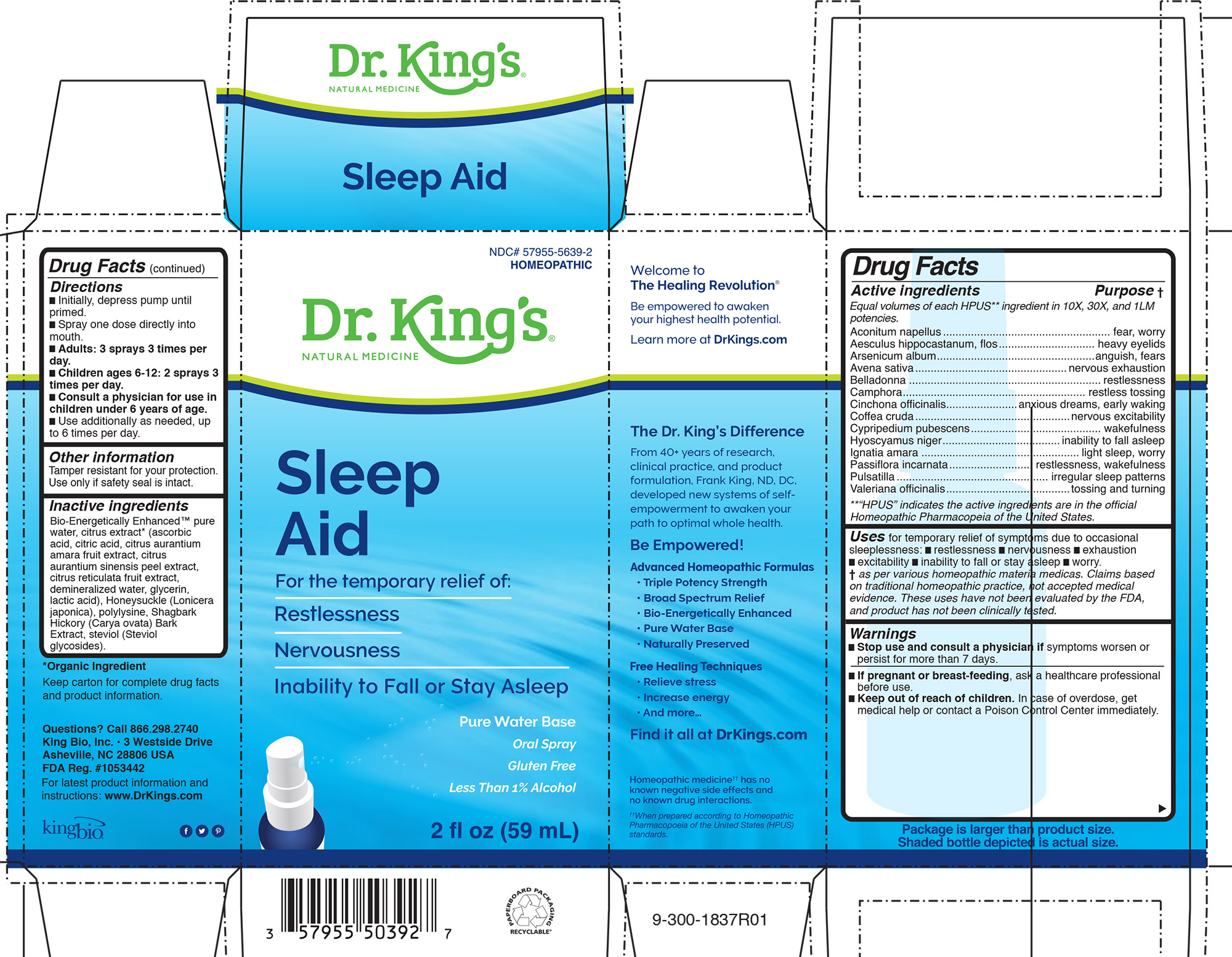 DRUG LABEL: Sleep Aid
NDC: 57955-5639 | Form: LIQUID
Manufacturer: King Bio Inc.
Category: homeopathic | Type: HUMAN OTC DRUG LABEL
Date: 20200820

ACTIVE INGREDIENTS: ACONITUM NAPELLUS 10 [hp_X]/59 mL; AESCULUS HIPPOCASTANUM FLOWER 10 [hp_X]/59 mL; ARSENIC TRIOXIDE 10 [hp_X]/59 mL; AVENA SATIVA FLOWERING TOP 10 [hp_X]/59 mL; ATROPA BELLADONNA 10 [hp_X]/59 mL; CAMPHOR (NATURAL) 10 [hp_X]/59 mL; CINCHONA OFFICINALIS BARK 10 [hp_X]/59 mL; ARABICA COFFEE BEAN 10 [hp_X]/59 mL; CYPRIPEDIUM PARVIFLORUM VAR. PUBESCENS ROOT 10 [hp_X]/59 mL; HYOSCYAMUS NIGER 10 [hp_X]/59 mL; STRYCHNOS IGNATII SEED 10 [hp_X]/59 mL; PASSIFLORA INCARNATA FLOWER 10 [hp_X]/59 mL; PULSATILLA VULGARIS 10 [hp_X]/59 mL; VALERIAN 10 [hp_X]/59 mL
INACTIVE INGREDIENTS: WATER; CARYA OVATA BARK; CITRUS BIOFLAVONOIDS; LONICERA JAPONICA FLOWER; POLYEPSILON-LYSINE (4000 MW); REBAUDIOSIDE A

Sleep Aid

Active Ingredients

HPUS active ingredients

Equal volumes of each ingredient in 10X, 30X, and 1LM potencies

Aconitum napellus, Aesculus hippocastanum, flos, Arsenicum album, Avena sativa, Belladonna, Camphora, Cinchona officinalis, Coffea cruda, Cypripedium pubescens, Hyoscyamus niger, Ignatia amara, Passiflora incarnata, Pulsatilla, Valeriana officinalis.

Inactive Ingredients

Bio-Energetically Enhanced™ pure
water, citrus extract* (ascorbic
acid, citric acid, citrus aurantium
amara fruit extract, citrus
aurantium sinensis peel extract,
citrus reticulata fruit extract,
demineralized water, glycerin,
lactic acid), Honeysuckle (Lonicera
japonica), polylysine, Shagbark
Hickory (Carya ovata) Bark
Extract, steviol (Steviol
glycosides).

Directions

█ Initially, depress pump until
primed.
█ Spray one dose directly into
mouth.
█ Adults: 3 sprays 3 times per
day.
█ Children ages 6-12: 2 sprays 3
times per day.
█ Consult a physician for use in
children under 6 years of age.
█ Use additionally as needed, up
to 6 times per day.

Warnings

█ Stop use and consult a physician if symptoms worsen or
persist for more than 7 days.

PREGNANCY OR BREAST FEEDING

█ If pregnant or breast-feeding, ask a healthcare professional
before use.

█ Keep out of reach of children. In case of overdose, get
medical help or contact a Poison Control Center immediately.

Other Information

Tamper resistant for your protection. Use only if safety seal is intact.

Purpose

HPUS active ingredients Purpose

Equal volumes of each HPUS** ingredient in 10X, 30X, and 1LM
potencies.

Aconitum napellus...................................fear, worry

Aesculus hippocastanum, flos....................heavy eyelids

Arsenicum album....................................anguish, fears

Avena sativa..........................................nervous exhaustion

Belladonna.............................................restlessness

Camphora.............................................restless tossing

Cinchona officinalis.................................anxious dreams, early waking

Coffea cruda.........................................nervous excitability

Cypripedium pubescens.........................wakefulness

Hyoscyamus niger.................................inability to fall asleep

Ignatia amara.........................................light sleep, worry

Passiflora incarnata................................restlessness, wakefulness

Pulsatilla................................................irregular sleep patterns

Valeriana officinalis................................tossing and turning

**“HPUS” indicates the active ingredients are in the official
Homeopathic Pharmacopeia of the United States.

INDICATIONS AND USAGE

Uses for temporary relief of symptoms due to occasional
sleeplessness: █ restlessness █ nervousness █ exhaustion
█ excitability █ inability to fall or stay asleep █ worry.
† as per various homeopathic materia medicas. Claims based
on traditional homeopathic practice, not accepted medical
evidence. These uses have not been evaluated by the FDA,
and product has not been clinically tested.

Questions? Call 866.298.2740
King Bio, Inc. • 3 Westside Drive
Asheville, NC 28806 USA
FDA Reg. #1053442

For latest product information and instructions: www.DrKings.com